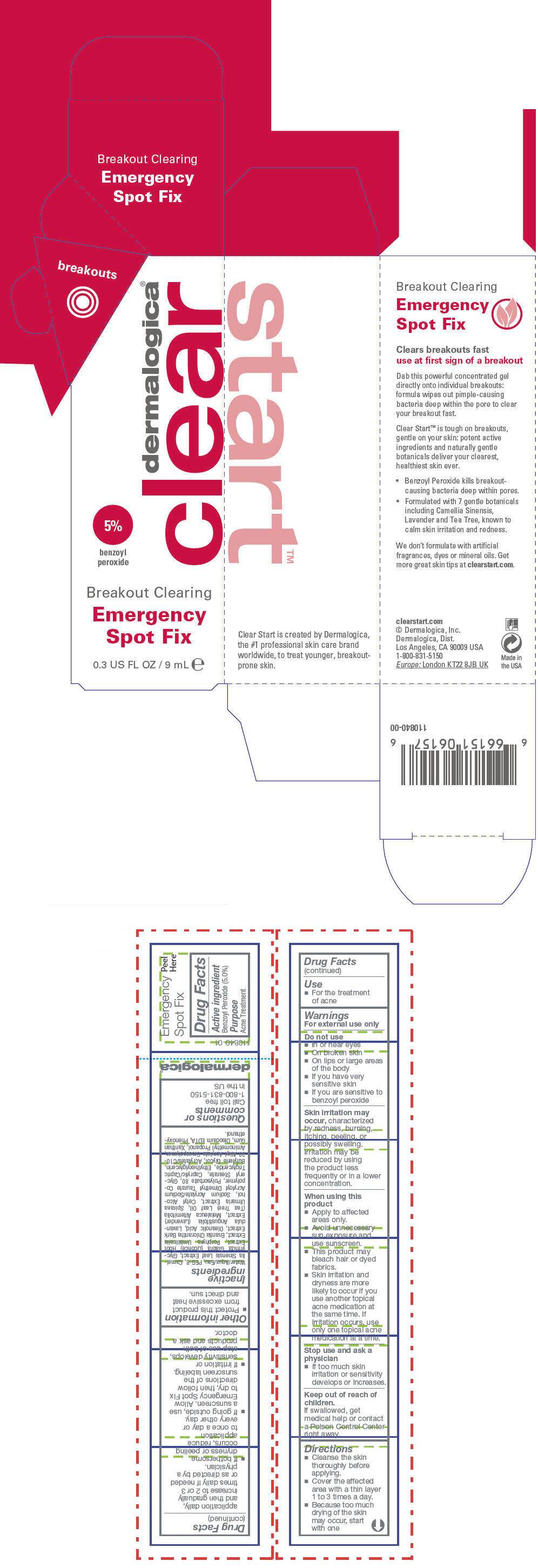 DRUG LABEL: Breakout Clearing Emergency Spot Fix
NDC: 68479-202 | Form: LOTION
Manufacturer: Dermalogica, Inc.
Category: otc | Type: HUMAN OTC DRUG LABEL
Date: 20140205

ACTIVE INGREDIENTS: Benzoyl Peroxide 50 mg/1 mL
INACTIVE INGREDIENTS: Water; Polyethylene Glycol 400; Green Tea Leaf; Glycyrrhiza Glabra; Porphyra Umbilicalis; Annickia Chlorantha Bark; Oleanolic Acid; Lavandula Angustifolia Flowering Top; Tea Tree Oil; Filipendula Ulmaria Root; Cetyl Alcohol; Sodium Acrylate/Sodium Acryloyldimethyltaurate Copolymer (4000000 MW); Polysorbate 80; Glyceryl Monostearate; Medium-Chain Triglycerides; Ethylhexylglycerin; Butylene Glycol; Carbomer Interpolymer Type A (Allyl Sucrose Crosslinked); Aminomethylpropanol; Xanthan Gum; Edetate Disodium; Phenoxyethanol

Breakout Clearing Emergency Spot Fix

Drug Facts

Active ingredient

Benzoyl Peroxide (5.0%)

Purpose

Acne Treatment

Use

- For the treatment of acne

Warnings

For external use only

Do not use

- In or near eyes
- On broken skin
- On lips or large areas of the body
- If you have very sensitive skin
- If you are sensitive to benzoyl peroxide

Skin irritation may occur, characterized by redness, burning, itching, peeling, or possibly swelling. Irritation may be reduced by using the product less frequently or in a lower concentration.

When using this product

- Apply to affected areas only.
- Avoid unnecessary sun exposure and use sunscreen.
- This product may bleach hair or dyed fabrics.
- Skin irritation and dryness are more likely to occur if you use another topical acne medication at the same time. If irritation occurs, use only one topical acne medication at a time.

Stop use and ask a physician

- If too much skin irritation or sensitivity develops or increases.

Keep out of reach of children.

If swallowed, get medical help or contact a Poison Control Center right away.

Directions

- Cleanse the skin thoroughly before applying.
- Cover the affected area with a thin layer 1 to 3 times a day.
- Because too much drying of the skin may occur, start with one application daily, and then gradually increase to 2 or 3 times daily if needed or as directed by a physician.
- If bothersome dryness or peeling occurs, reduce application to once a day or every other day.
- If going outside, use a sunscreen. Allow Emergency Spot Fix to dry, then follow directions of the sunscreen labeling.
- If irritation or sensitivity develops, stop use of both products and ask a doctor.

Other information

- Protect this product from excessive heat and direct sun.

Inactive ingredients

Water/Aqua/Eau, PEG-8, Camellia Sinensis Leaf Extract, Glycyrrhiza Glabra (Licorice) Root Extract, Porphyra Umbilicalis Extract, Enantia Chlorantha Bark Extract, Oleanolic Acid, Lavandula Angustifolia (Lavender) Extract, Melaleuca Alternifolia (Tea Tree) Leaf Oil, Spiraea Ulmaria Extract, Cetyl Alcohol, Sodium Acrylate/Sodium Acryloyl Dimethyl Taurate Copolymer, Polysorbate 80, Glyceryl Stearate, Caprylic/Capric Triglyceride, Ethylhexylglycerin, Butylene Glycol, Acrylates/C10-30 Alkyl Acrylate Crosspolymer, Aminomethyl Propanol, Xanthan Gum, Disodium EDTA, Phenoxyethanol.

Questions or comments

Call toll free 1-800-831-5150 in the US

PRINCIPAL DISPLAY PANEL - 9 mL Tube Carton

dermalogica®
clear

5%
benzoyl
peroxide

Breakout Clearing
Emergency
Spot Fix

0.3 US FL OZ / 9 mL e